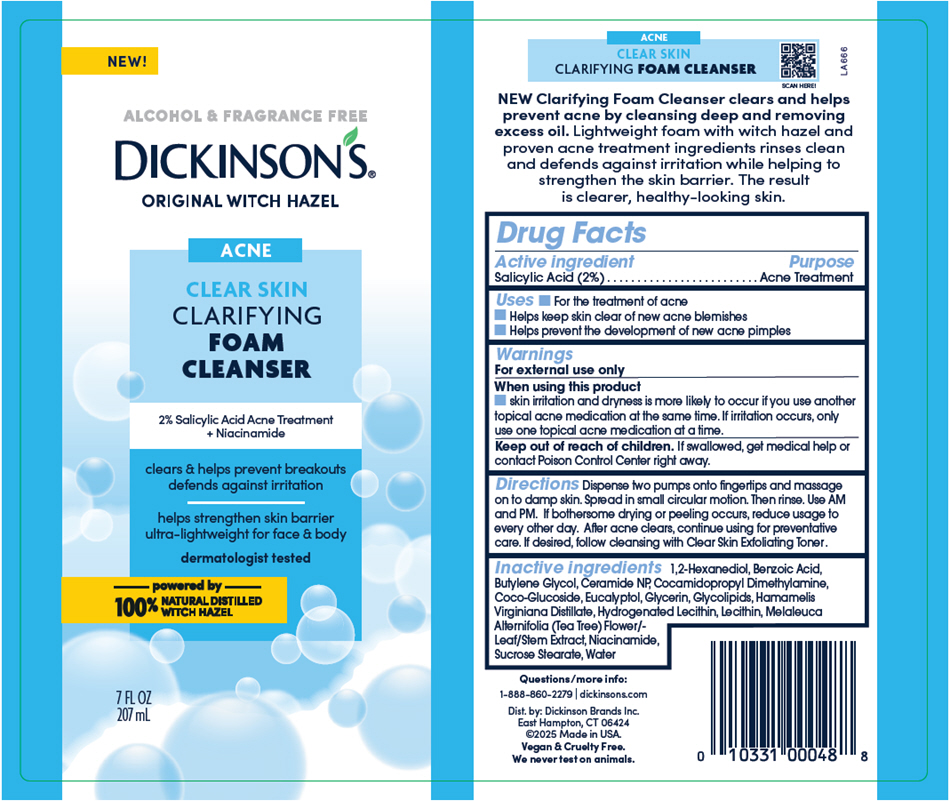 DRUG LABEL: Dickinsons Original Witch Hazel Clarifying Foam Cleanser
NDC: 52651-048 | Form: LIQUID
Manufacturer: Dickinson Brands Inc.
Category: otc | Type: HUMAN OTC DRUG LABEL
Date: 20250410

ACTIVE INGREDIENTS: SALICYLIC ACID 0.032 g/1.58 mL
INACTIVE INGREDIENTS: 1,2-HEXANEDIOL; BENZOIC ACID; BUTYLENE GLYCOL; CERAMIDE NP; COCAMIDOPROPYL DIMETHYLAMINE; COCO-GLUCOSIDE; EUCALYPTOL; GLYCERIN; HAMAMELIS VIRGINIANA TOP WATER; HYDROGENATED SOYBEAN LECITHIN; MELALEUCA ALTERNIFOLIA FLOWERING TOP; NIACINAMIDE; SUCROSE STEARATE; WATER

Dickinson's® Original Witch Hazel Clarifying Foam Cleanser

Drug Facts

Active ingredient

Salicylic Acid (2%)

Purpose

Acne Treatment

Uses

- For the treatment of acne
- Helps keep skin clear of new acne blemishes
- Helps prevent the development of new acne pimples

Warnings

For external use only

When using this product

- skin irritation and dryness is more likely to occur if you use another topical acne medication at the same time. If irritation occurs, only use one topical acne medication at a time.

Keep out of reach of children. If swallowed, get medical help or contact Poison Control Center right away.

Directions

Dispense two pumps onto ﬁngertips and massage on to damp skin. Spread in small circular motion. Then rinse. Use AM and PM. If bothersome drying or peeling occurs, reduce usage to every other day. After acne clears, continue using for preventative care. If desired, follow cleansing with Clear Skin Exfoliating Toner.

Inactive ingredients

1,2-Hexanediol, Benzoic Acid, Butylene Glycol, Ceramide NP, Cocamidopropyl Dimethylamine, Coco-Glucoside, Eucalyptol, Glycerin, Glycolipids, Hamamelis Virginiana Distillate, Hydrogenated Lecithin, Lecithin, Melaleuca Alternifolia (Tea Tree) Flower/Leaf/Stem Extract, Niacinamide, Sucrose Stearate, Water

Questions/more info:

1-888-860-2279 | dickinsons.com

Dist. by: Dickinson Brands Inc.
East Hampton, CT 06424

PRINCIPAL DISPLAY PANEL - 207 mL Bottle Label

NEW!

ALCOHOL & FRAGRANCE FREE
DICKINSON'S®
ORIGINAL WITCH HAZEL

ACNE
CLEAR SKIN
CLARIFYING
FOAM
CLEANSER

2% Salicylic Acid Acne Treatment
+ Niacinamide

clears & helps prevent breakouts
defends against irritation

helps strengthen skin barrier
ultra-lightweight for face & body

dermatologist tested

powered by
100% NATURAL DISTILLED
WITCH HAZEL

7 FL OZ
207 mL